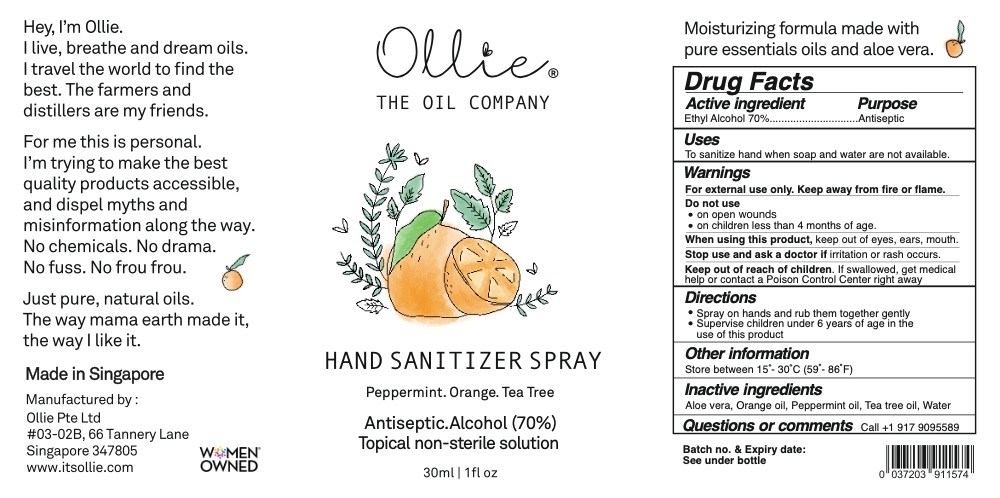 DRUG LABEL: Ollie Hand Sanitizer
NDC: 81634-001 | Form: LIQUID
Manufacturer: F.P. Aromatics Singapore Pte Ltd
Category: otc | Type: HUMAN OTC DRUG LABEL
Date: 20230411

ACTIVE INGREDIENTS: ALCOHOL 70 mL/100 mL
INACTIVE INGREDIENTS: WATER; ALOE VERA LEAF; ORANGE OIL; PEPPERMINT OIL; TEA TREE OIL

Active ingredient

Ethyl alcohol 70%

Purpose

Antiseptic

Uses

To sanitize hand when soap and water are not available.

Warnings

For external use only. Keep away from fire or flame.

Do not use

- on open wounds

- on children less than 4 months of age.

When using this product, keep out of eyes, ears, mouth.
Stop use and ask a doctor if irritation or rash occurs.
Keep out of reach of children. If swallowed, get medical help or contact a Poison Control Center right away

Direction

- Spray on hands and rub them together gently
- Supervise children under 6 years of age in the use of this product

Other information

Store between 15° - 30°C (59° - 86°F)

Inactive ingredient

Aloe vera, Orange oil, Peppermint oil, Tea tree oil, Water